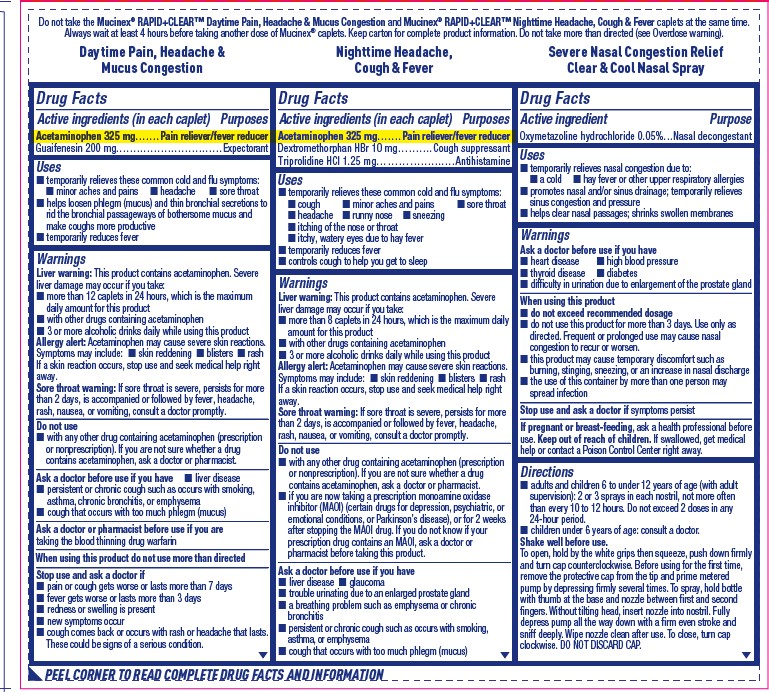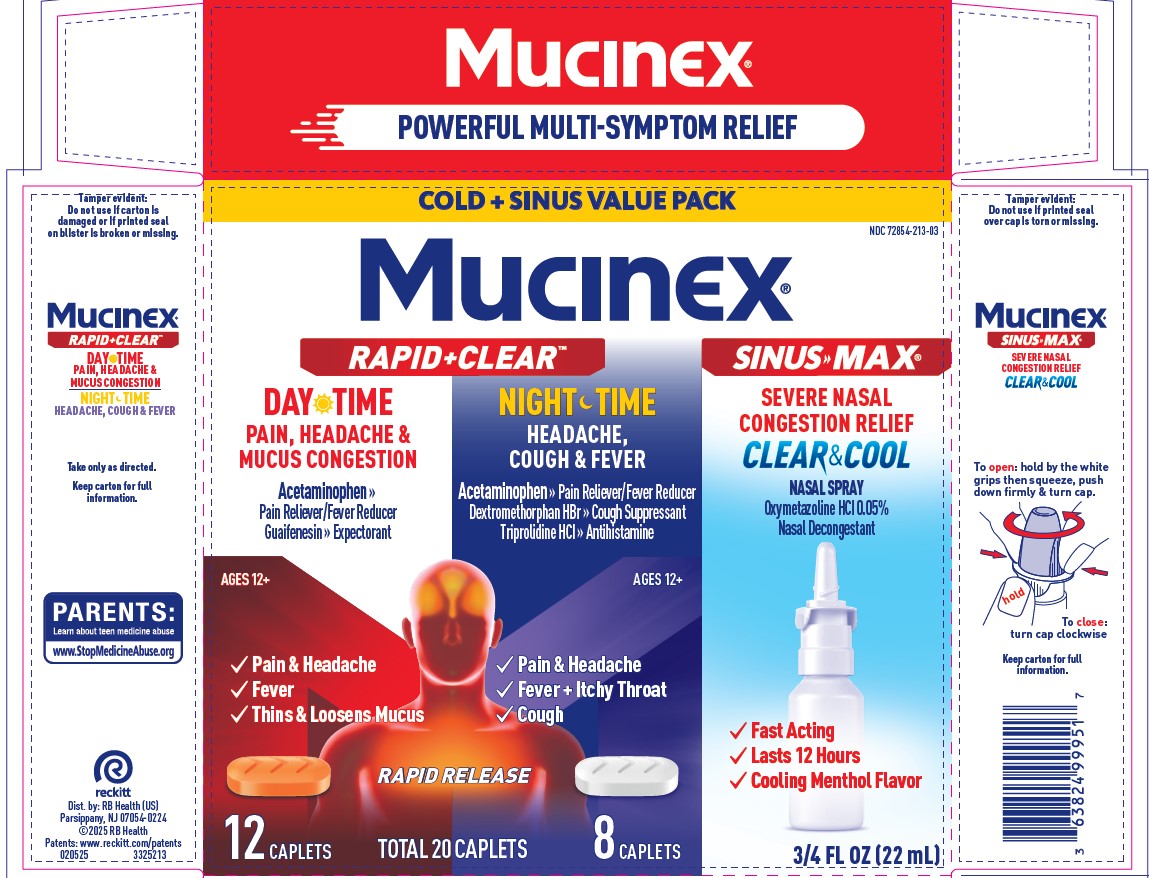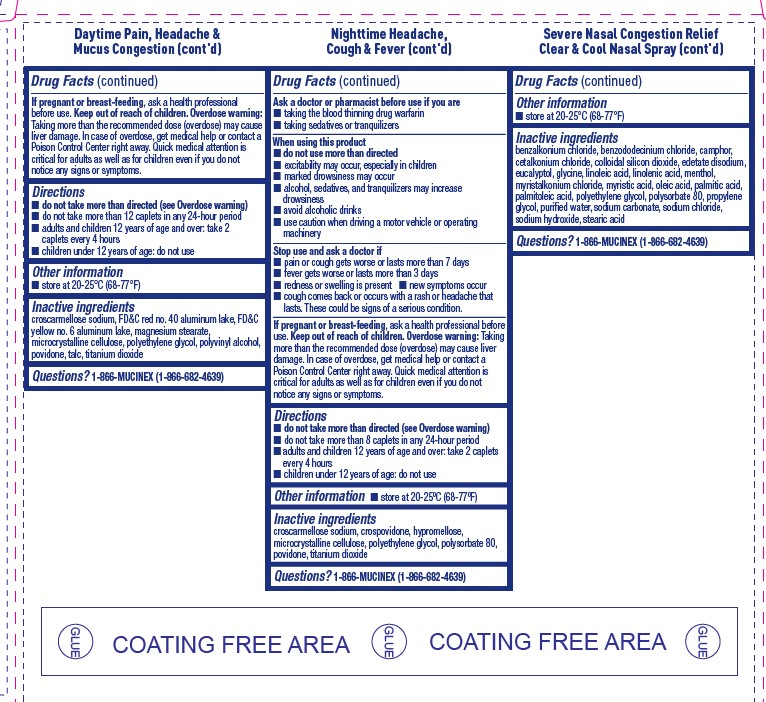 DRUG LABEL: MUCINEX Rapid Clear Day Night and Clear and Cool Nasal
NDC: 72854-213 | Form: KIT | Route: ORAL
Manufacturer: RB Health (US) LLC
Category: otc | Type: HUMAN OTC DRUG LABEL
Date: 20250618

ACTIVE INGREDIENTS: GUAIFENESIN 200 mg/1 1; ACETAMINOPHEN 325 mg/1 1; TRIPROLIDINE HYDROCHLORIDE 1.25 mg/1 1; DEXTROMETHORPHAN HYDROBROMIDE 10 mg/1 1; ACETAMINOPHEN 325 mg/1 1; OXYMETAZOLINE HYDROCHLORIDE 0.05 g/100 mL
INACTIVE INGREDIENTS: FD&C RED NO. 40 ALUMINUM LAKE; FD&C YELLOW NO. 6 ALUMINUM LAKE; POLYETHYLENE GLYCOL, UNSPECIFIED; TITANIUM DIOXIDE; POLYVINYL ALCOHOL; POVIDONE; CROSCARMELLOSE SODIUM; TALC; MAGNESIUM STEARATE; MICROCRYSTALLINE CELLULOSE; CROSCARMELLOSE SODIUM; CROSPOVIDONE, UNSPECIFIED; POLYSORBATE 80; POVIDONE; TITANIUM DIOXIDE; POLYETHYLENE GLYCOL, UNSPECIFIED; MICROCRYSTALLINE CELLULOSE; HYPROMELLOSE, UNSPECIFIED; CAMPHOR (NATURAL); BENZALKONIUM CHLORIDE; BENZODODECINIUM CHLORIDE

MUCINEX® Rapid Clear® Day Night Caplet + Clear & Cool Nasal Spray Combo

ACTIVE INGREDIENT

DAY

Acetaminophen 325 mg
Guaifenesin 200 mg

NIGHT

Acetaminophen 325 mg
Dextromethorphan HBr 10 mg
Triprolidine HCl 1.25 mg

SPRAY

Oxymetazoline hydrochloride 0.05%

PURPOSE

DAY

Acetaminophen 325 mg ........ Pain reliever/
fever reducer
Guaifenesin 200 mg.................... Expectorant

NIGHT

Acetaminophen 325 mg ........ Pain reliever/fever reducer
Dextromethorphan HBr 10 mg................Cough suppressant
Triprolidine HCl 1.25 mg...................................Antihistamine

SPRAY

Oxymetazoline hydrochloride 0.05% - Nasal decongestant

INDICATIONS AND USAGE

DAY

Uses
■ temporarily relieves these common cold and flu
symptoms:
■ minor aches and pains ■ headache
■ sore throat
■ helps loosen phlegm (mucus) and thin
bronchial secretions to rid the bronchial
passageways of bothersome mucus and make
coughs more productive
■ temporarily reduces fever

NIGHT

Uses
■ temporarily relieves these common cold and flu symptoms:
■ cough ■ minor aches and pains
■ sore throat ■ headache
■ runny nose ■ sneezing
■ itching of the nose or throat
■ itchy, watery eyes due to hay fever
■ temporarily reduces fever
■ controls cough to help you get to sleep

SPRAY

Uses

temporarily relieves nasal congestion due to:

- a cold
- hay fever or other upper respiratory allergies
- promotes nasal and sinus drainage
- temporarily relieves sinus congestion and pressure
- helps clear nasal passages; shrinks swollen membranes

WARNINGS

DAY

Warnings
Liver warning: This product contains acetaminophen.
Severe liver damage may occur if you take:
■ more than 12 caplets in 24 hours, which is
the maximum daily amount for this product
■ with other drugs containing acetaminophen
■ 3 or more alcoholic drinks daily while using
this product

Allergy alert: Acetaminophen may cause severe
skin reactions. Symptoms may include:
■ skin reddening ■ blisters ■ rash
If a skin reaction occurs, stop use and seek
medical help right away.

Sore throat warning: If sore throat is severe,
persists for more than 2 days, is accompanied
or followed by fever, headache, rash, nausea, or
vomiting, consult a doctor promptly.

Do not use
■ with any other drug containing acetaminophen
(prescription or nonprescription). If you are not
sure whether a drug contains acetaminophen,
ask a doctor or pharmacist.

Ask a doctor before use if you have
■ liver disease
■ persistent or chronic cough such as occurs
with smoking, asthma, chronic bronchitis, or
emphysema
■ cough that occurs with too much phlegm
(mucus)

Ask a doctor or pharmacist before use if you
are taking the blood thinning drug warfarin
When using this product do not use more
than directed

Stop use and ask a doctor if
■ pain or cough gets worse or lasts more than
7 days
■ fever gets worse or lasts more than 3 days
■ redness or swelling is present
■ new symptoms occur
■ cough comes back or occurs with rash or
headache that lasts. These could be signs of
a serious condition.

If pregnant or breast-feeding, ask a health
professional before use.
Overdose warning: Taking more than the
recommended dose (overdose) may cause liver
damage. In case of overdose, get medical help or
contact a Poison Control Center right away. Quick
medical attention is critical for adults as well as
for children even if you do not notice any signs or
symptoms.

NIGHT

Warnings
Liver warning: This product contains acetaminophen.
Severe liver damage may occur if you take:
■ more than 8 caplets in 24 hours, which is the maximum
daily amount for this product
■ with other drugs containing acetaminophen
■ 3 or more alcoholic drinks daily while using this product
Allergy alert: Acetaminophen may cause severe skin
reactions. Symptoms may include:
■ skin reddening ■ blisters ■ rash
If a skin reaction occurs, stop use and seek medical help right
away.

Sore throat warning: If sore throat is severe, persists for
more than 2 days, is accompanied or followed by fever,
headache, rash, nausea, or vomiting, consult a doctor
promptly.

Do not use
■ with any other drug containing acetaminophen
(prescription or nonprescription). If you are not sure
whether a drug contains acetaminophen, ask a doctor or
pharmacist.
■ if you are now taking a prescription monoamine oxidase
inhibitor (MAOI) (certain drugs for depression, psychiatric,
or emotional conditions, or Parkinson’s disease), or for
2 weeks after stopping the MAOI drug. If you do not know
if your prescription drug contains an MAOI, ask a doctor or
pharmacist before taking this product.

Ask a doctor before use if you have
■ liver disease ■ glaucoma
■ trouble urinating due to an enlarged prostate gland
■ a breathing problem such as emphysema or chronic
bronchitis
■ persistent or chronic cough such as occurs with
smoking, asthma, or emphysema

■ cough that occurs with too much phlegm (mucus)

Ask a doctor or pharmacist before use if you are
■ taking the blood thinning drug warfarin
■ taking sedatives or tranquilizers
When using this product
■ do not use more than directed
■ excitability may occur, especially in children
■ marked drowsiness may occur
■ alcohol, sedatives, and tranquilizers may increase drowsiness
■ avoid alcoholic drinks
■ use caution when driving amotor vehicle or operatingmachinery
Stop use and ask a doctor if
■ pain or cough gets worse or lasts more than 7 days
■ fever gets worse or lasts more than 3 days
■ redness or swelling is present
■ new symptoms occur
■ cough comes back or occurs with rash or headache
that lasts. These could be signs of a serious condition.

Overdose warning: Taking more than the recommended
dose (overdose) may cause liver damage. In case of overdose,
get medical help or contact a Poison Control Center right
away. Quick medical attention is critical for adults as well as
for children even if you do not notice any signs or symptoms.

SPRAY

Ask a doctor before use if you have

heart disease
high blood pressure
thyroid disease
diabetes
difficulty in urination due to enlargement of the prostate gland

When using this product

do not exceed recommended dosage
do not use this product for more than 3 days. Use only as directed. Frequent or prolonged use may cause nasal congestion to recur or worsen
this product may cause temporary discomfort such as burning, stinging, sneezing, or an increase in nasal discharge
the use of this container by more than one person may spread infection

Stop use and ask a doctor ifsymptoms persist

If pregnant or breast-feeding,ask a health professional before use.

DOSAGE AND ADMINISTRATION

DAY

Directions
■ do not take more than directed (see
Overdose warning)
■ do not take more than 12 caplets in any
24-hour period
■ adults and children 12 years of age and
over: take 2 caplets every 4 hours
■ children under 12 years of age: do not use

NIGHT

Directions
■ do not take more than directed (see Overdose warning)
■ do not take more than 8 caplets in any 24-hour period
■ adults and children 12 years of age and over: take
2 caplets every 4 hours
■ children under 12 years of age: do not use

SPRAY

adults and children 6 to under 12 years of age (with adult supervision): 2 or 3 sprays in each nostril, not more often than every 10 to 12 hours. Do not exceed 2 doses in any 24-hour period.
children under 6 years of age: consult a doctor.

Shake well before use.

To open, hold by the white grips then squeeze, push down
firmly and turn cap counterclockwise. Before using for the
first time, remove the protective cap from the tip and prime
metered pump by depressing firmly several times. To spray,
hold bottle with thumb at the base and nozzle between first
and second fingers. Without tilting head, insert nozzle into
nostril. Fully depress pump all the way down with a firm
even stroke and sniff deeply. Wipe nozzle clean after use.
To close, turn cap clockwise.
DO NOT DISCARD CAP.

OTHER SAFETY INFORMATION

DAY/NIGHT/SPRAY

Other information
■ store at 20-25°C (68-77°F)

INACTIVE INGREDIENT

DAY

Inactive ingredients
croscarmellose sodium, FD&C red no. 40
aluminum lake, FD&C yellow no. 6 aluminum
lake, magnesium stearate, microcrystalline
cellulose, polyethylene glycol, polyvinyl
alcohol, povidone, talc, titanium dioxide

NIGHT

Inactive ingredients
croscarmellose sodium, crospovidone, hypromellose,
microcrystalline cellulose, polyethylene glycol,
polysorbate 80, povidone, titanium dioxide

SPRAY

benzalkonium chloride,
benzododecinium chloride,
camphor

Questions? 1-866-MUCINEX
(1-866-682-4639)

Keep out of reach of children.

If pregnant or breast-feeding,ask a health professional before use.